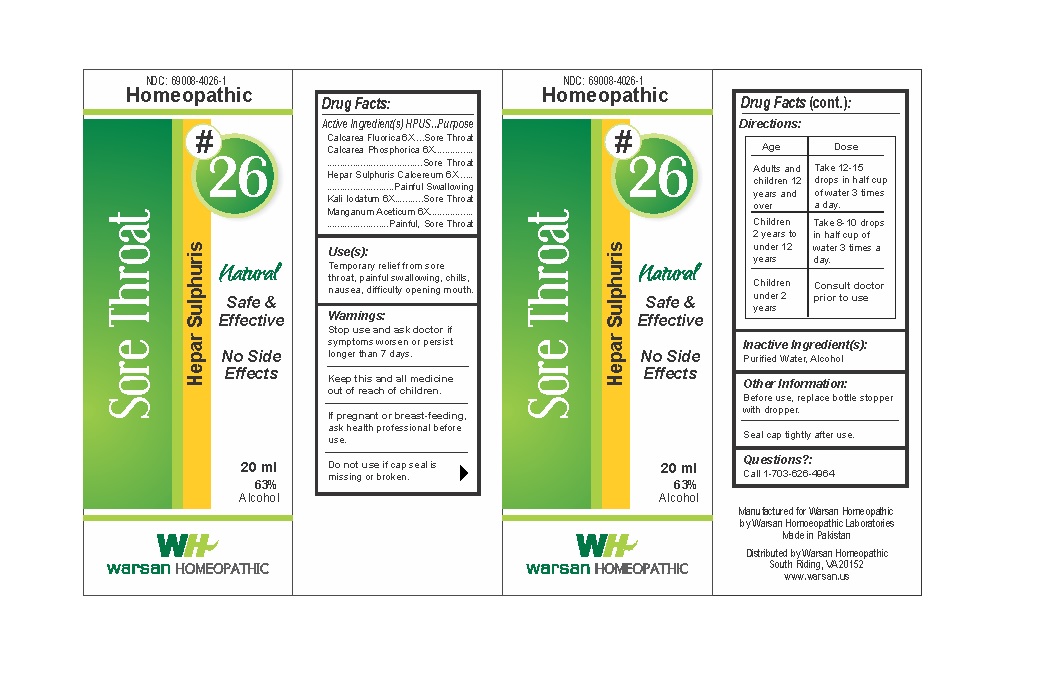 DRUG LABEL: Combination Remedy 26 - Sore Throat
NDC: 69008-4026 | Form: SOLUTION/ DROPS
Manufacturer: Warsan Homoeopathic Laboratories
Category: homeopathic | Type: HUMAN OTC DRUG LABEL
Date: 20171225

ACTIVE INGREDIENTS: CALCIUM SULFIDE 6 [hp_X]/1 mL; POTASSIUM IODIDE 6 [hp_X]/1 mL; CALCIUM FLUORIDE 6 [hp_X]/1 mL; TRIBASIC CALCIUM PHOSPHATE 6 [hp_X]/1 mL; MANGANESE ACETATE TETRAHYDRATE 6 [hp_X]/1 mL
INACTIVE INGREDIENTS: ALCOHOL; WATER

Stop use and ask doctor if symptoms worsen or persist longer than 7 days.

If pregnant or breast-feeding, ask health professional before use.

Do not use if tamper evident seal is missing or broken.

Keep out of reach of children.

ACTIVE INGREDIENT

Calcarea Fluorica 6X

Calcarea Phosphorica 6X

Hepar Sulphuris Calcereum 6X

Kali Iodatum 6X

Manganum Aceticum 6X

PURPOSE

Temporary relief from sore throat, painful swallowing, chills, nausea, difficulty opening mouth.

INACTIVE INGREDIENT

Purified Water

Alcohol

DOSAGE AND ADMINISTRATION

Adults and children 12 years and older: Take 10-15 drops in half cup of water 3 times a day.

Children 2 years to under 12 years: Take 8-10 drops in half cup of water of 3 times a day.

Children under 2 years: Consult doctor prior to use.

INDICATIONS AND USAGE

Temporary relief from sore throat, painful swallowing, chills, nausea, difficulty opening mouth.